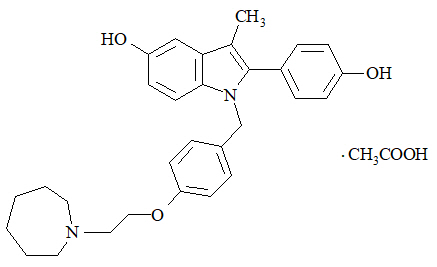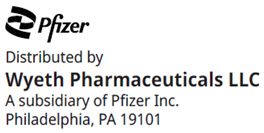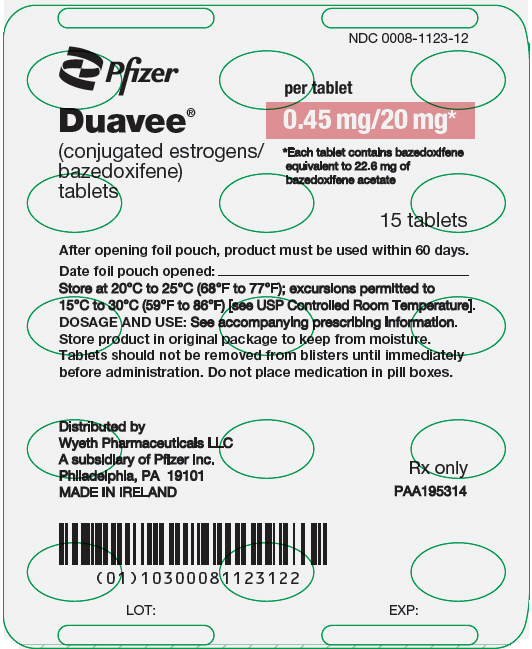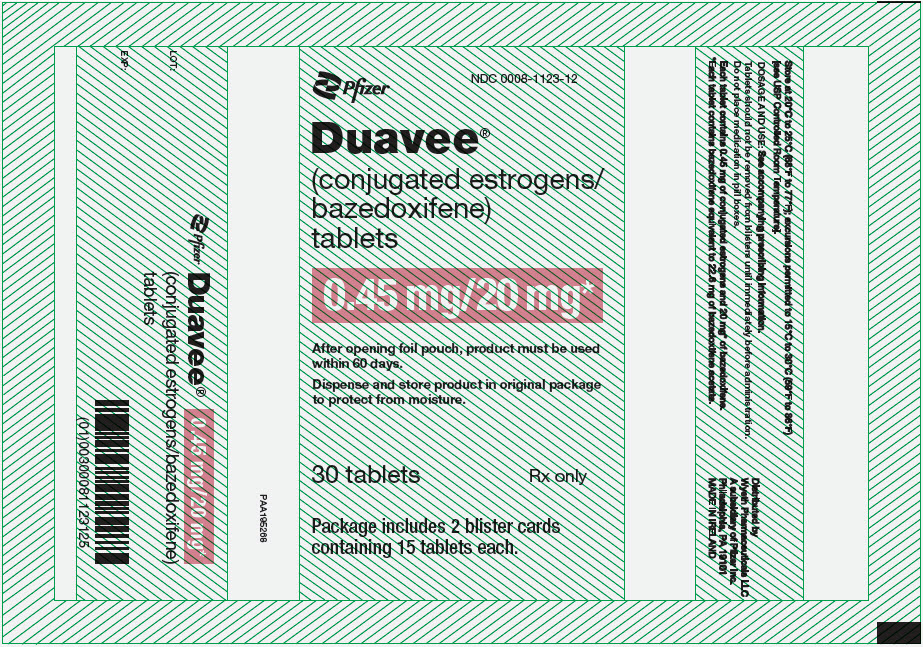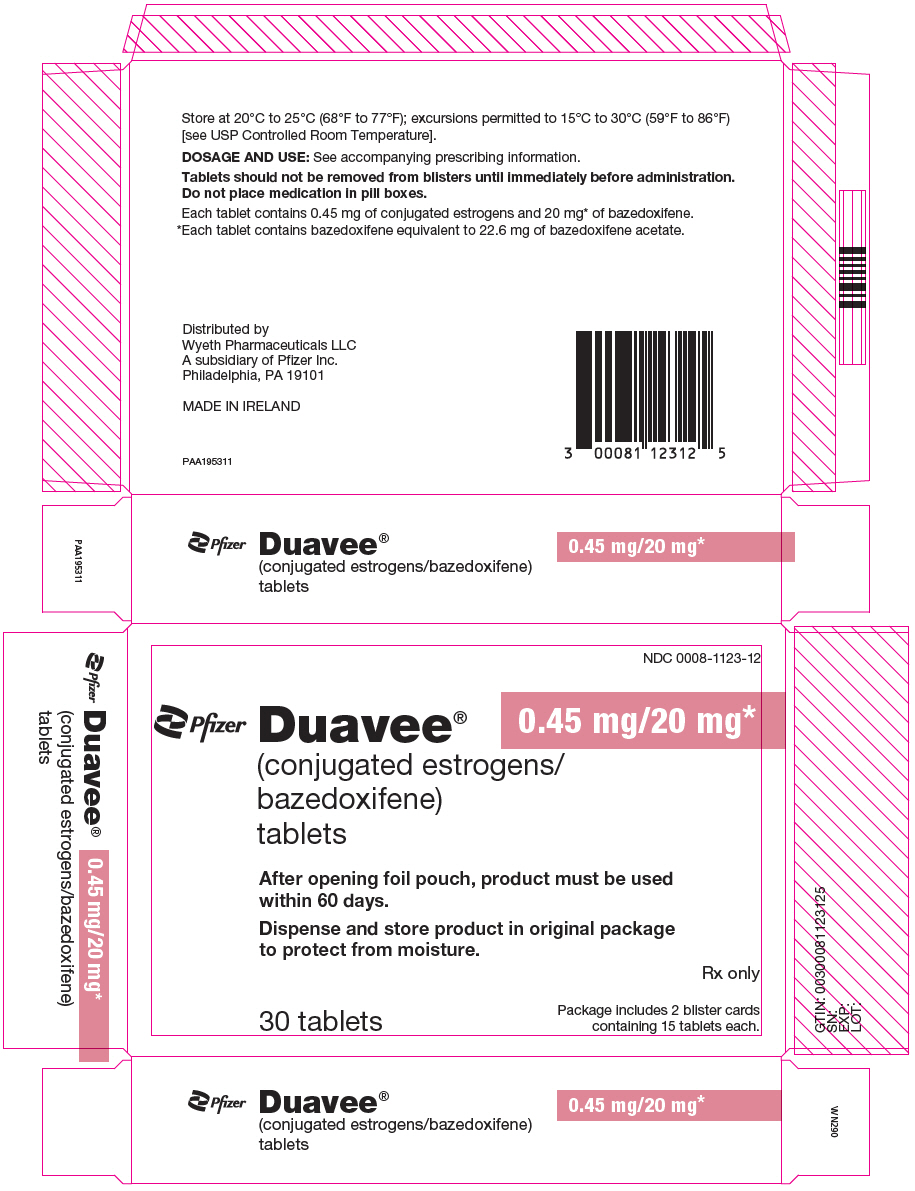 DRUG LABEL: Duavee
NDC: 0008-1123 | Form: TABLET, FILM COATED
Manufacturer: Wyeth Pharmaceuticals LLC, a subsidiary of Pfizer Inc.
Category: prescription | Type: HUMAN PRESCRIPTION DRUG LABEL
Date: 20250113

ACTIVE INGREDIENTS: ESTROGENS, CONJUGATED 0.45 mg/1 1; BAZEDOXIFENE ACETATE 20 mg/1 1
INACTIVE INGREDIENTS: TRIBASIC CALCIUM PHOSPHATE; HYDROXYPROPYL CELLULOSE (1600000 WAMW); MICROCRYSTALLINE CELLULOSE; POWDERED CELLULOSE; HYPROMELLOSE 2208 (100000 MPA.S); LACTOSE MONOHYDRATE; MAGNESIUM STEARATE; POLYETHYLENE GLYCOL 400; SUCROSE; ASCORBIC ACID; SUCROSE PALMITATE; HYDROXYETHYL CELLULOSE (100 MPA.S AT 2%); TITANIUM DIOXIDE; FERRIC OXIDE RED; FERRIC OXIDE YELLOW; FERROSOFERRIC OXIDE; POVIDONE, UNSPECIFIED; POLYDEXTROSE; MALTITOL; POLOXAMER 188; PROPYLENE GLYCOL; ISOPROPYL ALCOHOL

HIGHLIGHTS OF PRESCRIBING INFORMATION

These highlights do not include all the information needed to use DUAVEE safely and effectively. See full prescribing information for DUAVEE.
DUAVEE® (conjugated estrogens/bazedoxifene) tablets for oral use
Initial U.S. approval: 2013

WARNING: ENDOMETRIAL CANCER, CARDIOVASCULAR DISORDERS, AND PROBABLE DEMENTIA

See full prescribing information for complete Boxed Warning.

- Women taking DUAVEE should not take additional estrogens (5.1)
- There is an increased risk of endometrial cancer in a woman with a uterus who uses unopposed estrogens (5.1, 5.3)
- Estrogen therapy should not be used for the prevention of cardiovascular disease or dementia (5.2, 5.4)
- The Women's Health Initiative (WHI) estrogen-alone substudy reported increased risks of stroke and deep vein thrombosis (DVT) (5.2)
- The WHI Memory Study (WHIMS) estrogen-alone ancillary study of WHI reported an increased risk of probable dementia in postmenopausal women 65 years of age and older (5.4)

RECENT MAJOR CHANGES

Warnings and Precautions, Malignant Neoplasms (5.3) | 03/2024

1 INDICATIONS AND USAGE

DUAVEE is a combination of conjugated estrogens with an estrogen agonist/antagonist indicated for treatment of the following conditions in women with a uterus:

- Treatment of moderate to severe vasomotor symptoms associated with menopause (1.1)
- Prevention of postmenopausal osteoporosis (1.2)

Limitation of Use: DUAVEE should be used for the shortest duration consistent with treatment goals and risks for the individual woman (1.3)

2 DOSAGE AND ADMINISTRATION

- Take one tablet orally once daily (2)

3 DOSAGE FORMS AND STRENGTHS

Tablet containing conjugated estrogens 0.45 mg and bazedoxifene 20 mg (3)

4 CONTRAINDICATIONS

- Undiagnosed abnormal uterine bleeding (4, 5.3)
- Known, suspected, or past history of breast cancer (4, 5.3)
- Known or suspected estrogen-dependent neoplasia (4, 5.3)
- Active or past history of venous thromboembolism (4, 5.2)
- Active or past history of arterial thromboembolism (4, 5.2)
- Hypersensitivity (angioedema, anaphylaxis) to estrogens, bazedoxifene, or any ingredients (4)
- Known hepatic impairment or disease (4, 5.9, 8.7, 12.3)
- Known protein C, protein S, or antithrombin deficiency or other known thrombophilic disorders (4)
- Pregnancy (1, 4, 8.1)

5 WARNINGS AND PRECAUTIONS

- Women taking DUAVEE should not take progestins, additional estrogens or additional estrogen agonist/antagonists (5.1)
- Cardiovascular disorders, including venous thromboembolism, pulmonary embolism, stroke, and retinal vascular thrombosis (5.2, 5.6)
- Malignant neoplasms, including endometrial cancer, breast cancer, and ovarian cancer (5.3)
- Estrogens increase the risk of gallbladder disease (5.5)
- Discontinue estrogen if loss of vision, severe hypertriglyceridemia or cholestatic jaundice occurs (5.6, 5.8, 5.9)
- Monitor thyroid function in women on thyroid replacement therapy (5.10, 5.17)

6 ADVERSE REACTIONS

In four prospective, randomized, placebo-controlled trials the common adverse reactions (incidence ≥ 5%) were muscle spasms, nausea, diarrhea, dyspepsia, abdominal pain upper, oropharyngeal pain, dizziness, and neck pain (6.1)
To report SUSPECTED ADVERSE REACTIONS, contact Pfizer Inc. at 1-800-438-1985 or FDA at 1-800-FDA-1088 or www.fda.gov/medwatch.

8 USE IN SPECIFIC POPULATIONS

- Geriatric Use: DUAVEE was not studied in women aged 75 or older (8.5, 12.3); use in this population is not recommended (2.7, 8.5)
- An increased risk of probable dementia in women over 65 years of age was reported in the Women's Health Initiative Memory ancillary studies of the Women's Health Initiative (5.4, 8.5, 14.6)
- Renal Impairment: DUAVEE was not studied in women with renal impairment; use in this population is not recommended (2.6, 8.6, 12.3)

FULL PRESCRIBING INFORMATION

WARNING: ENDOMETRIAL CANCER, CARDIOVASCULAR DISORDERS, AND PROBABLE DEMENTIA

- Women taking DUAVEE should not take additional estrogens [see Warnings and Precautions (5.1)]
- There is an increased risk of endometrial cancer in a woman with a uterus who uses unopposed estrogens. DUAVEE has been shown to reduce the risk of endometrial hyperplasia, which may be a precursor to endometrial cancer. Adequate diagnostic measures, including directed or random endometrial sampling when indicated, should be undertaken to rule out malignancy in postmenopausal women with undiagnosed persistent or recurring abnormal genital bleeding [see Warnings and Precautions (5.3)]
- Estrogen therapy should not be used for the prevention of cardiovascular disease or dementia [see Warnings and Precautions (5.2, 5.4)]
- The Women's Health Initiative (WHI) estrogen-alone substudy reported increased risks of stroke and deep vein thrombosis (DVT) in postmenopausal women (50 to 79 years of age) during 7.1 years of treatment with daily oral conjugated estrogens (0.625 mg)-alone, relative to placebo [see Warnings and Precautions (5.2)]
- The WHI Memory Study (WHIMS) estrogen-alone ancillary study of WHI reported an increased risk of probable dementia in postmenopausal women 65 years of age and older during 5.2 years of treatment with daily conjugated estrogens (0.625 mg)-alone, relative to placebo. It is unknown whether this finding applies to younger postmenopausal women [see Warnings and Precautions (5.4)]

Only daily oral 0.625 mg CE was studied in the estrogen-alone substudy of the WHI. Therefore, the relevance of the WHI findings regarding adverse cardiovascular events and dementia to lower CE doses, other routes of administration, or other estrogen-alone products is not known. Without such data, it is not possible to definitively exclude these risks or determine the extent of these risks for other products. Discuss with your patient the benefits and risks of estrogen-alone therapy, taking into account her individual risk profile.

Estrogens should be prescribed at the lowest effective doses and for the shortest duration consistent with treatment goals and risks for the individual woman.

1 INDICATIONS AND USAGE

DUAVEE is indicated in women with a uterus for:

1.3 Important Limitations of Use

- Use DUAVEE for the shortest duration consistent with treatment goals and risks for the individual woman. Postmenopausal women should be re-evaluated periodically as clinically appropriate to determine if treatment is still necessary.
- When prescribing solely for the prevention of postmenopausal osteoporosis, therapy should only be considered for women at significant risk of osteoporosis and non-estrogen medication should be carefully considered.

2 DOSAGE AND ADMINISTRATION

2.1 Treatment of Moderate to Severe Vasomotor Symptoms Associated with Menopause

The recommended dosage is one DUAVEE tablet daily.

2.2 Prevention of Postmenopausal Osteoporosis

The recommended dosage is one DUAVEE tablet daily.

2.3 General Dosing Information

Take DUAVEE once daily, without regard to meals. Tablets should be swallowed whole.

2.4 Recommendations for Calcium and Vitamin D Supplementation

Women taking DUAVEE for prevention of postmenopausal osteoporosis should add supplemental calcium and/or vitamin D to their diet if daily intake is inadequate.

2.5 Administration Instructions for Missed Doses

If a dose of DUAVEE is missed, instruct patients to take it as soon as remembered unless it is almost time for the next scheduled dose. They should not take two doses at the same time.

2.6 Use in Patients with Renal Impairment

The pharmacokinetics of DUAVEE have not been evaluated in patients with renal impairment. Use in patients with renal impairment is not recommended [see Use in Specific Populations (8.6) and Clinical Pharmacology (12.3)].

2.7 Use in the Elderly

DUAVEE has not been studied in women over 75 years of age. Use in women over 75 years of age is not recommended.

3 DOSAGE FORMS AND STRENGTHS

DUAVEE (conjugated estrogens/bazedoxifene) tablets, 0.45 mg/20 mg are oval, biconvex, pink tablets, branded with "0.45/20" in black ink on one side.

4 CONTRAINDICATIONS

DUAVEE is contraindicated in women with any of the following conditions:

- Undiagnosed abnormal uterine bleeding
- Known, suspected, or past history of breast cancer
- Known or suspected estrogen-dependent neoplasia
- Active deep venous thrombosis, pulmonary embolism, or history of these conditions
- Active arterial thromboembolic disease (for example, stroke, myocardial infarction) or history of these conditions
- Hypersensitivity (for example, anaphylaxis, angioedema) to estrogens, bazedoxifene, or any ingredients
- Known hepatic impairment or disease
- Known protein C, protein S, or antithrombin deficiency or other known thrombophilic disorders
- Pregnancy, as DUAVEE may cause fetal harm [see pregnancy (8.1)].

5 WARNINGS AND PRECAUTIONS

5.1 Drugs Containing Progestins, Estrogens or Estrogen Agonist/Antagonists

DUAVEE contains conjugated estrogens and bazedoxifene, an estrogen agonist/antagonist. Women taking DUAVEE should not take progestins, additional estrogens or additional estrogen agonist/antagonists.

5.2 Cardiovascular Disorders

Estrogen agonist/antagonists (including bazedoxifene, a component of DUAVEE) and estrogens individually are known to increase the risk of VTE.

An increased risk of stroke and DVT has been reported with estrogen-alone therapy. Should any of these occur or be suspected, DUAVEE should be discontinued immediately.

Risk factors for arterial vascular disease (for example, hypertension, diabetes mellitus, tobacco use, hypercholesterolemia, and obesity) and/or VTE (for example, personal history or family history of VTE, obesity, and systemic lupus erythematosus) should be managed appropriately.

Stroke

In the WHI estrogen-alone substudy, a statistically significant increased risk of stroke was reported in women 50 to 79 years of age receiving daily conjugated estrogens (CE) (0.625 mg)-alone compared to women in the same age group receiving placebo (45 versus 33 per 10,000 women-years). The increase in risk was demonstrated in year 1 and persisted [see Clinical Studies (14.5)].

Subgroup analyses of women 50 to 59 years of age suggest no increased risk of stroke for those women receiving conjugated estrogens (0.625 mg)-alone versus those receiving placebo (18 versus 21 per 10,000 women-years).

Should a stroke occur or be suspected, DUAVEE should be discontinued immediately [see Contraindications (4)].

Coronary Heart Disease

In the WHI estrogen-alone substudy, no overall effect on coronary heart disease (CHD) events (defined as nonfatal myocardial infarction, silent myocardial infarction, or CHD death) was reported in women receiving estrogen-alone compared to placebo [see Clinical Studies (14.5)].

Subgroup analyses of women 50 to 59 years of age suggest a statistically non-significant reduction in CHD events (CE [0.625 mg]-alone compared to placebo) in women with less than 10 years since menopause (8 versus 16 per 10,000 women-years).

Venous Thromboembolism (VTE)

In the WHI estrogen-alone substudy, the risk of VTE [DVT and pulmonary embolism (PE)] was increased for women receiving daily conjugated estrogens (0.625 mg)-alone compared to placebo (30 versus 22 per 10,000 women-years), although only the increased risk of DVT reached statistical significance (23 versus 15 per 10,000 women-years). The increase in VTE risk was demonstrated during the first 2 years [see Clinical Studies (14.5)].

If feasible, DUAVEE should be discontinued at least 4 to 6 weeks before surgery of the type associated with an increased risk of thromboembolism, or during periods of prolonged immobilization. Because immobilization increases the risk for venous thromboembolic events independent of therapy, DUAVEE should be discontinued prior to and during prolonged immobilization (e.g., post-surgical recovery, prolonged bed rest) and DUAVEE therapy should be resumed only after the patient is fully ambulatory. In addition, women taking DUAVEE should be advised to move about periodically during travel involving prolonged immobilization.

5.3 Malignant Neoplasms

Endometrial Cancer

An increased risk of endometrial cancer has been reported with the use of unopposed estrogen therapy in women with a uterus. The reported endometrial cancer risk among unopposed estrogen users is about 2 to 12 times greater than in non-users, and appears dependent on duration of treatment and on estrogen dose. Most studies show no significant increased risk associated with use of estrogens for less than 1 year. The greatest risk appears associated with prolonged use, with increased risks of 15- to 24-fold for 5 to 10 years or more of treatment. This risk has been shown to persist for at least 8 to 15 years after estrogen therapy is discontinued.

DUAVEE contains an estrogen agonist/antagonist. This component reduces the risk of endometrial hyperplasia that can occur with the conjugated estrogens component. Endometrial hyperplasia may be a precursor to endometrial cancer. Women taking DUAVEE should not take additional estrogens as this may increase the risk of endometrial hyperplasia.

Clinical surveillance of all women taking DUAVEE is important. Adequate diagnostic measures, including directed or random endometrial sampling when indicated, should be undertaken to rule out malignancy in postmenopausal women with undiagnosed persistent or recurring abnormal genital bleeding.

Breast Cancer

The WHI substudy of daily conjugated estrogens (0.625 mg)-alone provided information about breast cancer in estrogen‑alone users. In the WHI estrogen-alone substudy, after an average follow-up of 7.1 years, daily conjugated estrogen (0.625 mg)-alone was not associated with an increased risk of invasive breast cancer (relative risk [RR] 0.80).

The use of estrogen-alone has been reported to result in an increase in abnormal mammograms requiring further evaluation. The effect of treatment with DUAVEE on the risk of breast cancer is unknown.

All women should receive yearly breast examinations by a healthcare provider and perform monthly breast self-examinations. In addition, mammography examinations should be scheduled based on patient age, risk factors, and prior mammogram results.

Ovarian Cancer

A meta-analysis of 17 prospective and 35 retrospective epidemiology studies found that women who used hormonal therapy for menopausal symptoms had an increased risk for ovarian cancer. The primary analysis, using case-control comparisons, included 12,110 cancer cases from the 17 prospective studies. The relative risks associated with current use of hormonal therapy was 1.41 (95% confidence interval [CI] 1.32 to 1.50); there was no difference in the risk estimates by duration of the exposure (less than 5 years [median of 3 years] vs. greater than 5 years [median of 10 years] of use before the cancer diagnosis). The relative risk associated with combined current and recent use (discontinued use within 5 years before cancer diagnosis) was 1.37 (95% CI 1.27–1.48), and the elevated risk was significant for both estrogen-alone and estrogen plus progestin products. The exact duration of hormone therapy use associated with an increased risk of ovarian cancer, however, is unknown.

The effect of treatment with DUAVEE on the risk of ovarian cancer is unknown.

5.4 Probable Dementia

In the WHIMS estrogen-alone ancillary study of WHI, a population of 2,947 hysterectomized women 65 to 79 years of age was randomized to daily CE (0.625 mg)-alone or placebo.

After an average follow-up of 5.2 years, 28 women in the estrogen-alone group and 19 women in the placebo group were diagnosed with probable dementia. The relative risk of probable dementia for CE-alone versus placebo was 1.49 (95 percent CI, 0.83–2.66). The absolute risk of probable dementia for CE-alone versus placebo was 37 versus 25 cases per 10,000 women-years [see Use in Specific Populations (8.5) and Clinical Studies (14.6)].

5.5 Gallbladder Disease

A 2- to 4-fold increase in the risk of gallbladder disease requiring surgery in postmenopausal women receiving estrogens has been reported.

5.6 Visual Abnormalities

Retinal vascular thrombosis has been reported in patients receiving estrogens. Discontinue medication pending examination if there is sudden partial or complete loss of vision, or a sudden onset of proptosis, diplopia, or migraine. If examination reveals papilledema or retinal vascular lesions, DUAVEE should be permanently discontinued.

5.7 Elevated Blood Pressure

In a small number of case reports in women receiving estrogens, substantial increases in blood pressure have been attributed to idiosyncratic reactions to estrogens. In a large, randomized, placebo-controlled clinical study, a generalized effect of estrogens on blood pressure was not seen.

5.8 Hypertriglyceridemia

In women with pre-existing hypertriglyceridemia, treatment with estrogens may be associated with elevations of plasma triglycerides leading to pancreatitis. Consider discontinuation of DUAVEE if pancreatitis occurs.

5.9 Hepatic Impairment and Past History of Cholestatic Jaundice

DUAVEE has not been studied in women with impaired liver function or past history of cholestatic jaundice.

Estrogens may be poorly metabolized in women with impaired liver function.

On average, women with hepatic impairment treated with bazedoxifene alone showed a 4.3-fold increase in overall exposures compared with controls [see Use in Specific Populations (8.7) and Clinical Pharmacology (12.3)].

For women with a history of cholestatic jaundice associated with past estrogen use or with pregnancy, caution should be exercised; and in the case of recurrence, DUAVEE should be discontinued. Use of DUAVEE in patients with hepatic impairment is contraindicated [see Contraindications (4)].

5.10 Hypothyroidism

Estrogen administration leads to increased thyroid-binding globulin (TBG) levels. Women with normal thyroid function can compensate for the increased TBG by making more thyroid hormone, thus maintaining free T4 and T3 serum concentrations in the normal range. Women dependent on thyroid hormone replacement therapy who are also receiving estrogens may require increased doses of their thyroid replacement therapy. These women should have their thyroid function monitored in order to maintain their free thyroid hormone levels in an acceptable range.

5.11 Fluid Retention

Estrogens may cause some degree of fluid retention. Because of this, patients who have conditions that might be influenced by this factor, such as cardiac dysfunction or renal impairment, warrant careful observation when estrogens are prescribed. Use of DUAVEE in patients with renal impairment is not recommended [see Use in Specific Populations (8.6)].

5.12 Hypocalcemia

Estrogen therapy should be used with caution in women with hypoparathyroidism as estrogen-induced hypocalcemia may occur.

5.13 Hereditary Angioedema

Exogenous estrogens may exacerbate symptoms of angioedema in women with hereditary angioedema.

5.14 Exacerbation of Other Conditions

Estrogens may cause an exacerbation of asthma, diabetes mellitus, epilepsy, migraine or porphyria, systemic lupus erythematosus, and hepatic hemangiomas and should be used with caution in women with these conditions.

5.15 Premenopausal Women

There is no indication for premenopausal use of DUAVEE. The efficacy and safety of DUAVEE in premenopausal women have not been established, and its use is not recommended. Additionally, there is concern regarding inadvertent drug exposure in pregnancy in women of reproductive potential who become pregnant, due to risk of fetal harm [see Use in Specific Populations (8.1)].

5.16 Laboratory Tests

Serum follicle stimulating hormone (FSH) and estradiol levels have not been shown to be useful in the management of moderate to severe vasomotor symptoms.

5.17 Drug-Laboratory Test Interactions

Accelerated prothrombin time, partial thromboplastin time, and platelet aggregation time; increased platelet count; increased factors II, VII antigen, VIII antigen, VIII coagulant activity, IX, X, XII, VII-X complex, II-VII-X complex, and beta-thromboglobulin; decreased levels of antifactor Xa and antithrombin III, decreased antithrombin III activity; increased levels of fibrinogen and fibrinogen activity; increased plasminogen antigen and activity.

Increased thyroid-binding globulin (TBG) leading to increased circulating total thyroid hormone, as measured by protein-bound iodine (PBI), T4 levels (by column or by radioimmunoassay), or T3 levels by radioimmunoassay. T3 resin uptake is decreased, reflecting the elevated TBG. Free T4 and free T3 concentrations are unaltered. Women on thyroid replacement therapy may require higher doses of thyroid hormone.

Other binding proteins may be elevated in serum, for example, corticosteroid binding globulin (CBG), sex hormone-binding globulin (SHBG), leading to increased total circulating corticosteroids and sex steroids, respectively. Free hormone concentrations, such as testosterone and estradiol, may be decreased. Other plasma proteins may be increased (angiotensinogen/renin substrate, alpha-1-antitrypsin, ceruloplasmin).

Increased plasma high-density lipoprotein (HDL) and HDL2 cholesterol subfraction concentrations, reduced low-density lipoprotein (LDL) cholesterol concentrations, increased triglyceride levels.

Impaired glucose tolerance.

6 ADVERSE REACTIONS

The following adverse reactions are discussed in greater detail in other sections of the label:

- Cardiovascular Disorders [see Warnings and Precautions (5.2)]
- Malignant Neoplasms [see Warnings and Precautions (5.3)]
- Gallbladder Disease [see Warnings and Precautions (5.5)]
- Hypertriglyceridemia [see Warnings and Precautions (5.8)]

6.1 Clinical Trials Experience

Because clinical trials are conducted under widely varying conditions, adverse reaction rates observed in the clinical trials of a drug cannot be directly compared to rates in the clinical trials of another drug and may not reflect the rates observed in clinical practice.

The safety of conjugated estrogens/bazedoxifene was evaluated in four Phase 3 clinical trials ranging from 12 weeks to 24 months in duration and enrolling 6,210 postmenopausal women age 40 to 75 years (mean age 55 years). A total of 1,224 patients were treated with DUAVEE and 1,069 patients received placebo. Women enrolled in Studies 1 and 2 received calcium (600–1200 mg) and vitamin D (200–400 IU) daily, while women in Studies 3 and 4 received no calcium and vitamin D supplementation as part of the protocol.

The incidence of all-cause mortality was 0.0% in the DUAVEE group and 0.2% in the placebo group. The incidence of serious adverse reactions was 3.5% in the DUAVEE group and 4.8% in the placebo group. The percentage of patients who withdrew from treatment due to adverse reactions was 7.5% in the DUAVEE group and 10.0% in the placebo group. The most common adverse reactions leading to discontinuation were hot flush, abdominal pain upper, and nausea.

The most commonly observed adverse reactions (incidence ≥ 5%) more frequently reported in women treated with DUAVEE than placebo are presented in Table 1.

Table 1: Adverse Reactions (Incidence ≥ 5%) More Common in the DUAVEE Treatment Group in Placebo-controlled Trials
 | DUAVEE (N=1224) n (%) | Placebo (N=1069) n (%)
Gastrointestinal disorders
Nausea | 100 (8) | 58 (5)
Diarrhea | 96 (8) | 57 (5)
Dyspepsia | 84 (7) | 59 (6)
Abdominal pain upper | 81 (7) | 58 (5)
Musculoskeletal and connective tissue disorders
Muscle spasms | 110 (9) | 63 (6)
Neck pain | 62 (5) | 46 (4)
Nervous system disorders
Dizziness | 65 (5) | 37 (3)
Respiratory, thoracic, and mediastinal disorders
Oropharyngeal pain | 80 (7) | 61 (6)

Venous thromboembolism: In the clinical studies with DUAVEE, the reporting rates for venous thromboembolism (deep venous thrombosis, pulmonary embolism, and retinal vein thrombosis) were low in all treatment groups. Adverse reactions of venous thromboembolism were reported in 0.0% of patients treated with DUAVEE and 0.1% of patients treated with placebo. Due to the low rate of events in both groups, it is not possible to conclude that the risk of venous thromboembolism with DUAVEE is different from that seen with other estrogen therapies [see Warnings and Precautions (5.2)].

7 DRUG INTERACTIONS

7.1 Cytochrome P450 (CYP)

In vitro and in vivo studies have shown that estrogens are metabolized partially by cytochrome P450 3A4 (CYP3A4). Concomitant administration of itraconazole, a strong CYP3A4 inhibitor, with DUAVEE, resulted in increases in bazedoxifene exposure (40%) and, to a lesser extent, conjugated estrogens exposure (9% for baseline-adjusted total estrone, 5% for total equilin), compared to DUAVEE alone [see Pharmacokinetics (12.3)]. Inducers of CYP3A4, such as St. John's Wort (Hypericum perforatum) preparations, phenobarbital, carbamazepine, and rifampin, may reduce plasma concentrations of some estrogens, possibly resulting in a decrease in therapeutic effects and/or changes in the uterine bleeding profile.

Bazedoxifene does not induce or inhibit the activities of major CYP isoenzymes. In vitro data suggest that bazedoxifene is unlikely to interact with co-administered drugs via CYP-mediated metabolism.

7.2 Uridine Diphosphate Glucuronosyltransferase (UGT)

Bazedoxifene undergoes metabolism by UGT enzymes in the intestinal tract and liver. The metabolism of bazedoxifene may be increased by concomitant use of substances known to induce UGTs, such as rifampin, phenobarbital, carbamazepine, and phenytoin. A reduction in bazedoxifene exposure may be associated with an increase risk of endometrial hyperplasia. Adequate diagnostic measures, including directed or random endometrial sampling when indicated, should be undertaken to rule out malignancy in postmenopausal women with undiagnosed persistent or recurring abnormal genital bleeding.

7.3 Atorvastatin

Concomitant administration of bazedoxifene (40 mg daily) and atorvastatin (20 mg, single-dose) to healthy postmenopausal women did not affect the pharmacokinetics of bazedoxifene, atorvastatin or its active metabolites.

8 USE IN SPECIFIC POPULATIONS

8.1 Pregnancy

Risk Summary

DUAVEE is contraindicated for use in pregnant women and is not indicated for use in females of reproductive potential [see Contraindications (4), Warnings and Precautions (5.15)].

Conjugated Estrogens (CE)

There are no data with the use of conjugated estrogens in pregnant women; however, epidemiologic studies and meta-analyses have not found an increased risk of genital and non-genital birth defects (including cardiac anomalies and limb-reduction defects) following exposure to combined hormonal contraceptives before conception or during early pregnancy.

Bazedoxifene

There are no available data on bazedoxifene use in pregnant women to inform a drug associated risk of adverse developmental outcomes. Animal studies have shown that oral bazedoxifene administered during the period of organogenesis to pregnant rats or rabbits at 0.3 and 2 times, respectively, the exposure at the maximum recommended dose, can cause fetal harm [see Data]. Based on mechanism of action, bazedoxifene may block the important functions that estrogen has during all stages of pregnancy [see Clinical Pharmacology (12.1)].

Data

Animal data

Bazedoxifene

Administration of bazedoxifene to rats at maternally toxic dosages ≥1 mg/kg/day (≥ 0.3 times the human area under the curve (AUC) at the 20 mg dose) resulted in reduced numbers of live fetuses and/or reductions in fetal body weights. No fetal developmental anomalies were observed. In studies conducted with pregnant rabbits treated with bazedoxifene, abortion and an increased incidence of heart (ventricular septal defect) and skeletal system (ossification delays, misshapen or misaligned bones, primarily of the spine and skull) anomalies in the fetuses were present at maternally toxic dosages of ≥ 0.5 mg/kg/day (≥ 2 times the human AUC at the 20 mg dose).

8.2 Lactation

Risk Summary

DUAVEE is not indicated for use in females of reproductive potential [see Warnings and Precautions (5.15)].

Conjugated Estrogens

Estrogens are present in human milk and can reduce milk production in breast-feeding females. This reduction can occur at any time but is less likely to occur once breast-feeding is well-established.

Bazedoxifene

There are no data on the presence of bazedoxifene in either human or animal breast milk, the effect on the breastfed infant, or the effects on milk production. Based on mechanism of action, bazedoxifene may block the important functions that estrogen has in mammary tissue during lactation [see Clinical Pharmacology (12.1)].

8.3 Females and Males of Reproductive Potential

Infertility

Bazedoxifene

Based on animal data, bazedoxifene administration may adversely affect female fertility. However, clinical fertility studies with bazedoxifene have not been conducted [see Nonclinical Toxicology (13.1)].

8.4 Pediatric Use

DUAVEE is not indicated for use in children [see Indications and Usage (1)].

8.5 Geriatric Use

DUAVEE is not recommended for use in women greater than 75 years of age [see Dosage and Administration (2.7) and Clinical Pharmacology 12.3)].

Of the total number of women in phase 3 clinical studies who received DUAVEE, 4.60% (n=224) were 65 years and over. DUAVEE was not studied in women aged 75 and over. No overall differences in safety or effectiveness were observed between women 65–74 years of age and younger women, and other reported clinical experience has not identified differences in responses between the elderly and younger women, but greater sensitivity of some older women cannot be ruled out.

An increased risk of probable dementia in women over 65 years of age was reported in the Women's Health Initiative Memory ancillary studies of the Women's Health Initiative using daily conjugated estrogens (0.625 mg) [see Clinical Studies (14.6)].

8.6 Renal Impairment

DUAVEE is not recommended for use in patients with renal impairment [see Dosage and Administration (2.6) and Clinical Pharmacology (12.3)].

The pharmacokinetics, safety, and efficacy of DUAVEE have not been evaluated in women with renal impairment.

8.7 Hepatic Impairment

DUAVEE is contraindicated in patients with hepatic impairment [see Contraindications (4) and Clinical Pharmacology (12.3)].

The pharmacokinetics, safety, and efficacy of DUAVEE have not been evaluated in women with hepatic impairment. In a pharmacokinetics study of bazedoxifene 20 mg alone, the Cmax and AUC of bazedoxifene increased 67% and 143%, respectively, in women with mild hepatic impairment (Child Pugh Class A), compared to healthy women. The Cmax and AUC of bazedoxifene increased 32% and 109%, respectively, in women with moderate hepatic impairment (Child Pugh Class B). The Cmax and AUC of bazedoxifene increased 20% and 268%, respectively, in women with severe hepatic impairment (Child Pugh Class C).

No pharmacokinetic studies with conjugated estrogens were conducted in women with hepatic impairment.

8.8 Body Mass Index (BMI)

Following DUAVEE administration, the systemic exposures of conjugated estrogens and bazedoxifene were lower in obese subjects, compared to non-obese subjects [see Pharmacokinetics (12.3)].

A single dose of DUAVEE (conjugated estrogens 0.45 mg/bazedoxifene 20 mg) was administered to 12 obese BMI ≥ 30 [mean (SD) = 32.7 (2.7) kg/m^2] and 12 non-obese BMI < 30 [mean (SD) 25.3 (2.6) kg/m^2] postmenopausal women. In obese subjects, systemic exposures of total estrone, total equilin, and bazedoxifene were 2%, 32%, and 13% lower, respectively, compared to non-obese subjects.

A greater reduction in bazedoxifene exposure compared to conjugated estrogens may be associated with decreased protection from endometrial hyperplasia. Monitor and evaluate women with postmenopausal or unexplained genital bleeding for possible endometrial hyperplasia or malignancy [see Warnings and Precautions (5.3)].

10 OVERDOSAGE

In case of overdosage, there is no specific antidote, and the treatment should be symptomatic.

Symptoms of overdosage of estrogen-containing products in adults and children may include nausea, vomiting, breast tenderness, dizziness, abdominal pain, drowsiness/fatigue; withdrawal bleeding may occur.

11 DESCRIPTION

DUAVEE (conjugated estrogens/bazedoxifene), contains conjugated estrogens with bazedoxifene, an estrogen agonist/antagonist.

Conjugated estrogens are purified from pregnant mares' urine and consist of the sodium salts of water-soluble estrogen sulfates blended to represent the average composition of material derived from pregnant mares' urine. Conjugated estrogens are a mixture of sodium estrone sulfate and sodium equilin sulfate, and also contain as concomitant components, sodium sulfate conjugates, 17α-dihydroequilin, 17α-estradiol, and 17β-dihydroequilin.

Bazedoxifene is supplied as the acetate salt (bazedoxifene acetate) and has the chemical name 1H-Indol-5-ol, 1-[[4-[2-(hexahydro-1H-azepin-1-yl) ethoxy]phenyl]methyl]-2-(4-hydroxyphenyl)-3-methyl-, monoacetate. The empirical formula is C30H34N2O3 ∙ C2H4O2, and the molecular weight is 530.65.

Bazedoxifene acetate is a white to tan powder. The aqueous solubility of bazedoxifene is pH-dependent. Solubility is higher at lower pH. The solubility of bazedoxifene acetate in unbuffered sterile water was measured to be 923 microgramsA/mL at pH 5.4. The following represents the chemical structure of bazedoxifene acetate:

DUAVEE is available for oral administration as tablets containing 0.45 mg of conjugated estrogens with 20 mg of bazedoxifene (equivalent to 22.6 mg of bazedoxifene acetate). Each tablet of DUAVEE contains the following inactive ingredients: calcium phosphate tribasic, hydroxypropyl cellulose, microcrystalline cellulose, powdered cellulose, hypromellose, lactose monohydrate, magnesium stearate, polyethylene glycol, sucrose, ascorbic acid, sucrose palmitic acid ester, hydroxyethylcellulose, titanium dioxide, red iron oxide, yellow iron oxide, black iron oxide, povidone, polydextrose, maltitol, poloxamer 188, propylene glycol, and isopropyl alcohol.

12 CLINICAL PHARMACOLOGY

12.1 Mechanism of Action

DUAVEE pairs conjugated estrogens with bazedoxifene. Conjugated estrogens and bazedoxifene function by binding to and activating estrogen receptors (ER) α and β, which vary in proportion from tissue to tissue. Conjugated estrogens are composed of multiple estrogens and are agonists of ER- α and β. Bazedoxifene is an estrogen agonist/antagonist that acts as an agonist in some estrogen-sensitive tissues and an antagonist in others (e.g., uterus). The pairing of conjugated estrogens with bazedoxifene produces a composite effect that is specific to each target tissue. The bazedoxifene component reduces the risk of endometrial hyperplasia that can occur with the conjugated estrogens component.

12.2 Pharmacodynamics

Generally, a serum estrogen concentration does not predict an individual woman’s therapeutic response to DUAVEE nor her risk for adverse outcomes. Likewise, exposure comparisons across different estrogen products to infer efficacy or safety for the individual woman may not be valid.

12.3 Pharmacokinetics

Absorption

Following administration of multiple doses of conjugated estrogens 0.45 mg/bazedoxifene 20 mg to healthy women who were naturally postmenopausal or who had undergone bilateral oophorectomy, the mean steady state pharmacokinetic parameters at Day 10 for conjugated estrogens (baseline adjusted for total estrone) and bazedoxifene are summarized in Table 2.

Table 2: Mean ± SD Steady-State Pharmacokinetic Parameters (n=24)
 | Cmax (ng/mL) | Tmax (hr) | AUCss (ng∙hr/mL)
Baseline-Adjusted Total Estrone | 2.6 ± 0.8 | 6.5 ± 1.6 | 35 ± 12
Bazedoxifene | 6.9 ± 3.9 | 2.5 ± 2.1 | 71 ± 34

Results from monotherapy studies with conjugated estrogens or bazedoxifene components of DUAVEE, are noted below:

Conjugated estrogens are soluble in water and are well-absorbed from the gastrointestinal tract after release from the drug formulation.

Bazedoxifene exhibits a linear increase in plasma concentrations for single doses from 0.5 mg up to 120 mg and multiple daily doses from 1 mg to 80 mg. The absolute bioavailability of bazedoxifene is approximately 6%.

Food Effect

In a single-dose, crossover study in 23 postmenopausal women given conjugated estrogens 0.625 mg/bazedoxifene 20 mg with a high fat/high calorie meal, food increased AUC0–inf of bazedoxifene by 25%. The Cmax of bazedoxifene was unchanged.

Distribution

The distribution of conjugated estrogens and bazedoxifene after administration of DUAVEE has not been studied.

Results from monotherapy studies with conjugated estrogens or bazedoxifene, components of DUAVEE, are noted below:

The distribution of exogenous estrogens is similar to that of endogenous estrogens. Estrogens are widely distributed in the body and are generally found in higher concentrations in the sex hormone target organs. Estrogens circulate in the blood largely bound to sex hormone binding globulin (SHBG) and albumin.

Following intravenous (IV) administration of a 3 mg dose of bazedoxifene, the volume of distribution is 14.7 ± 3.9 L/kg. Bazedoxifene is highly bound (98%–99%) to plasma proteins in vitro, but does not bind to SHBG.

Metabolism

The metabolic disposition of conjugated estrogens and bazedoxifene, after administration of DUAVEE, has not been studied.

Results from monotherapy studies with conjugated estrogens or bazedoxifene, components of DUAVEE, are noted below:

Exogenous estrogens are metabolized in the same manner as endogenous estrogens. Circulating estrogens exist in a dynamic equilibrium of metabolic interconversions. 17-β estradiol is converted reversibly to estrone, and both can be converted to estriol, which is the major urinary metabolite. In postmenopausal women, a significant proportion of the circulating estrogens exists as sulfate conjugates, especially estrone sulfate, which serves as a circulating reservoir for the formation of more active estrogens.

The metabolic disposition of bazedoxifene has been determined following oral administration of 20 mg of radiolabeled bazedoxifene. Bazedoxifene is extensively metabolized in women. Glucuronidation is the major metabolic pathway. Little or no cytochrome P450-mediated metabolism is evident. Bazedoxifene-5-glucuronide is the major circulating metabolite. The concentrations of this glucuronide are approximately 10-fold higher than those of unchanged drug in plasma.

Excretion

After administration of a single dose of conjugated estrogens/bazedoxifene, baseline-adjusted total estrone (representing conjugated estrogens) is eliminated with a half-life of approximately 17 hours. Bazedoxifene is eliminated with a half-life of approximately 30 hours. Steady-state concentrations are achieved by the second week of once-daily administration.

Results from monotherapy studies with conjugated estrogens or bazedoxifene, components of DUAVEE, are noted below:

The conjugated estrogens components, 17β-estradiol, estrone, and estriol are excreted in the urine, along with glucuronide and sulfate conjugates.

The clearance of bazedoxifene is 0.4 ± 0.1 L/h/kg based on intravenous administration. The major route of excretion after oral administration of 20 mg of radiolabeled bazedoxifene is via biliary excretion, followed by elimination in the feces (~85%), with < 1% of the radioactive dose eliminated in the urine. Based on these results, it is expected that bazedoxifene undergoes entero-hepatic recycling from the gut back to the systemic circulation, therefore, some drugs may potentially interfere with bazedoxifene recycling process in the gut by various mechanisms resulting in a decrease in its systemic exposure.

Use in Specific Populations

Pediatric

The pharmacokinetics of conjugated estrogens/bazedoxifene tablets have not been evaluated in a pediatric population [see Use in Specific Populations (8.4)].

Geriatric

The effect of age on the pharmacokinetics of conjugated estrogens/bazedoxifene tablets have not been evaluated [see Use in Specific Populations (8.5)].

No pharmacokinetic studies with conjugated estrogens were conducted in specific populations, including women over 75 years of age.

The pharmacokinetics of a 20 mg single-dose of bazedoxifene, were evaluated in postmenopausal women. On average, compared to women 51 to 64 years of age (n=8), women 65 to 74 years of age (n=8) showed a 1.5-fold increase in AUC, and women ≥ 75 years of age (n=8) showed a 2.6-fold increase in AUC.

Renal Impairment

The pharmacokinetics of conjugated estrogens/bazedoxifene tablets have not been evaluated in women with renal impairment [see Dosage and Administration (2.6) and Use in Specific Populations (8.6)].

Hepatic Impairment

The pharmacokinetics of conjugated estrogens/bazedoxifene tablets have not been evaluated in women with hepatic impairment [see Contraindications (4), Warnings and Precautions (5.5), and Use in Specific Populations (8.7)].

No pharmacokinetic studies with conjugated estrogens were conducted in specific populations, including women with hepatic impairment.

A single dose of bazedoxifene 20 mg was given to fasted, healthy (N=18) and hepatically impaired postmenopausal women. In six mild hepatic impairment patients (Child Pugh Class A), Cmax and AUC of bazedoxifene increased 67% and 143%, respectively, compared to healthy subjects. In six moderate hepatic impairment patients (Child Pugh Class B), Cmax and AUC of bazedoxifene increased 32% and 109%, respectively, compared to healthy subjects. In six severe hepatic impairment patients (Child Pugh Class C), Cmax and AUC of bazedoxifene increased 20% and 268%, respectively, compared to healthy subjects. Half-life was prolonged from 32 to 50 hrs in patients with severe hepatic impairment, compared to healthy subjects.

Body Mass Index

In a clinical study, a single dose of DUAVEE (conjugated estrogens 0.45 mg/bazedoxifene 20 mg) was administered to 12 obese [mean (SD) BMI = 32.7 (2.7) kg/m^2] and 12 non-obese [mean (SD) BMI = 25.3 (2.6) kg/m^2] postmenopausal women. In obese subjects, systemic exposure (AUC0–72) of total estrone was 2% lower and systemic exposures (AUC0–inf) of total equilin and bazedoxifene were 32% and 13% lower, respectively, compared to non-obese subjects.

Drug Interactions

Effect of Co-Administered Drugs on the Pharmacokinetics of Conjugated Estrogens/Bazedoxifene

In a drug-drug interaction study, itraconazole 200 mg, a strong CYP3A4 inhibitor, was administered with breakfast to 24 postmenopausal women for 4 days, followed by a fifth dose of itraconazole 200 mg with breakfast and DUAVEE on Day 5 (3 hours after itraconazole). Itraconazole 200 mg was continued for 2 additional days after the co-administration of itraconazole 200 mg and DUAVEE. Following co-administration of DUAVEE and itraconazole, baseline-adjusted total estrone Cmax and AUC0–72 increased 9% and 9%, respectively, total equilin Cmax and AUC0–72 increased 11% and 5%, respectively, and bazedoxifene Cmax and AUC0–inf increased 11% and 40%, respectively, compared to subjects treated with DUAVEE alone.

Effect of Co-Administered Drugs on the Pharmacokinetics of Bazedoxifene

Conjugated Estrogens

Conjugated estrogens 0.625 mg were administered alone for 6 consecutive days prior to the co-administration of a single dose of 20 mg bazedoxifene and conjugated estrogens 0.625 mg in thirty postmenopausal women. Conjugated estrogens 0.625 mg were continued for 2 additional days after the co-administration of bazedoxifene and conjugated estrogens. The Cmax of bazedoxifene increased by 3% and AUC of bazedoxifene decreased by 6%.

Ibuprofen

A single dose of ibuprofen 600 mg was given with a bazedoxifene 20 mg capsule in twelve postmenopausal women after an overnight fast. Co-administration of ibuprofen and bazedoxifene increased Cmax and AUC of bazedoxifene by 18% and 7%, respectively.

Atorvastatin

Atorvastatin 20 mg was given once with bazedoxifene 40 mg in thirty postmenopausal women. Co-administration of atorvastatin and bazedoxifene decreased Cmax of bazedoxifene by 3% and increased AUC of bazedoxifene by 6%.

Azithromycin

Azithromycin 500 mg was given once daily for 8 consecutive days in thirty postmenopausal women. Azithromycin 500 mg and a bazedoxifene 40 mg tablet were co-administered on Day 9. Azithromycin 250 mg administration once daily continued on Days 10 to 13. Co-administration of azithromycin and bazedoxifene increased Cmax of bazedoxifene by 6% and decreased AUC of bazedoxifene by 15%.

Aluminum and Magnesium Hydroxide

A single dose of 460 mg aluminum hydroxide and 400 mg magnesium hydroxide was given with a bazedoxifene 40 mg tablet in thirty postmenopausal women after an overnight fast. Co-administration of aluminum/magnesium hydroxide and bazedoxifene decreased Cmax of bazedoxifene by 8% and increased AUC of bazedoxifene by 7%.

Effect of Bazedoxifene on the Pharmacokinetics of Co-Administered Drugs

Conjugated Estrogens

Bazedoxifene 20 mg was administered alone for 8 consecutive days prior to co-administration of a single dose of conjugated estrogens 0.625 mg and bazedoxifene 20 mg in twenty-six postmenopausal women. Bazedoxifene 20 mg was continued for 2 additional days after co-administration of bazedoxifene and conjugated estrogens. The Cmax and AUC of unconjugated estrone increased by 11% and 3%, respectively. The Cmax and AUC of unconjugated equilin increased by 17% and 14%, respectively.

Ibuprofen

A single dose of bazedoxifene 20 mg capsule was given with a single dose of ibuprofen 600 mg in twelve fasted, postmenopausal women. Co-administration of bazedoxifene and ibuprofen increased the Cmax of ibuprofen by 6%. The AUC of ibuprofen was unchanged.

Atorvastatin

Bazedoxifene 40 mg was given for 8 consecutive days prior to co-administration of bazedoxifene 40 mg and atorvastatin 20 mg. Co-administration of bazedoxifene and atorvastatin decreased Cmax of atorvastatin by 14%. The AUC of atorvastatin was unchanged. The Cmax and AUC of 2-OH atorvastatin were decreased by 18% and 8%, respectively.

13 NONCLINICAL TOXICOLOGY

13.1 Carcinogenesis, Mutagenesis, Impairment of Fertility

Carcinogenesis

Carcinogenicity studies with conjugated estrogens/bazedoxifene have not been conducted.

Long-term continuous administration of natural and synthetic estrogens in certain animal species increases the frequency of carcinomas of the breast, uterus, cervix, vagina, testis, and liver.

In 6-month oral gavage carcinogenicity studies of bazedoxifene in transgenic Tg.RasH2 mice, there was a drug-related increased incidence of benign, ovarian granulosa-cell tumors in female mice given 150 or 500 mg/kg/day. In a two-year dietary carcinogenicity study of bazedoxifene in rats (administered at 0.003%, 0.01%, 0.03%, or 0.1%) a drug-related marked increased incidence of benign, ovarian granulosa-cell tumors was observed in female rats at concentrations of 0.03% and 0.1%. Systemic exposure (AUC) of bazedoxifene in these groups was 3 and 8 times that observed in postmenopausal women administered 20 mg/day. In male rats, drug-related renal tumors (adenomas and carcinomas), in the presence of renal toxicity, were observed at all doses tested, which corresponded to exposure ratios of 0.06 to 5 times the clinical AUC at a dose of 20 mg.

Mutagenesis

Mutagenicity studies with conjugated estrogens/bazedoxifene have not been conducted.

Bazedoxifene was not genotoxic or mutagenic in a battery of tests, including in vitro bacterial reverse mutation assay, in vitro mammalian cell forward mutation assay at the thymidine kinase (TK+/-) locus in L5178Y mouse lymphoma cells, in vitro chromosome aberration assay in Chinese hamster ovary (CHO) cells, and in vivo mouse micronucleus assay.

Impairment of Fertility

Impairment of fertility studies with conjugated estrogens/bazedoxifene have not been conducted.

Female rats were administered daily dosages of 0.3 to 30 mg/kg bazedoxifene (0.03 to 10 times human AUC at the 20 mg dose) prior to and during mating with untreated males. Estrous cycles and fertility were adversely affected in all bazedoxifene-treated female groups.

13.2 Animal Toxicology and/or Pharmacology

In a 12-month study in ovariectomized rats, co-administration of conjugated estrogens (2.5 mg/kg/day) and bazedoxifene (0.1, 0.3, or 1 mg/kg/day) prevented the loss of bone mass at the spine, femur, and tibia with concomitant maintenance of biomechanical strength parameters.

14 CLINICAL STUDIES

14.1 Treatment of Moderate to Severe Vasomotor Symptoms Associated with Menopause in Women with a Uterus

The safety and efficacy of DUAVEE as a treatment for moderate to severe vasomotor symptoms associated with menopause was established in a 12-week randomized, double-blind, placebo-controlled study (Study 3). Study 3 enrolled a total of 318 women, age 42–64 (mean age of 53 years), who had at least 7 moderate to severe hot flushes per day or at least 50 per week at baseline. The mean number of years since menopause was 4.5 years with all women undergoing natural menopause. A total of 127 women were assigned to DUAVEE and 63 women were assigned to placebo.

In Study 3, DUAVEE significantly reduced the number and severity of moderate to severe hot flushes, as measured by the daily severity score, compared with placebo at Weeks 4 and 12. The change from baseline in the number and severity of moderate to severe hot flushes observed and the difference from placebo in Study 3 are shown in Table 3.

Table 3: Adjusted Mean Change from Baseline in the Average Daily Frequency and Severity of Hot Flushes (Study 3)
 | Frequency |  | Severity
 | DUAVEE | Placebo | DUAVEE | Placebo
N | 122 | 63 | 122 | 63
Baseline | 10.3 | 10.5 | 2.3 | 2.3
Week 4
Mean Change [Change from baseline using ANCOVA model] | -5.9 | -2.8 | -0.6 | -0.1
Treatment Difference [Based on raw data analysis using ANCOVA model: Difference= Treatment + Baseline + Site] | -3.1 (-4.4, -1.7) [p<0.001] | -- | -0.5 (-0.7, -0.3) | --
Week 12
Mean Change | -7.6 | -4.9 | -0.9 | -0.3
Treatment Difference | -2.7 (-3.8, -1.6) | -- | -0.6 (-0.9, -0.4) | --

14.2 Prevention of Postmenopausal Osteoporosis in Women with a Uterus

The safety and efficacy of DUAVEE for the prevention of postmenopausal osteoporosis was demonstrated in Study 1 and Study 2.

Study 1 was a 24-month, double-blind, randomized, placebo- and active-controlled study evaluating the safety and efficacy of multiple combinations of conjugated estrogen/bazedoxifene (including conjugated estrogens 0.45 mg/bazedoxifene 20 mg) compared to placebo. The primary endpoint of the study was the incidence of endometrial hyperplasia at Year 1. Bone mineral density change at the lumbar spine at Year 2 was the key secondary endpoint, assessed in two subsets of patients (Substudy I and Substudy II). Patients enrolled into Substudy I had to be more than 5 years postmenopausal, have a lumbar spine or total hip T-score of -1 to -2.5, and have at least one additional risk factor for osteoporosis (e.g., Caucasian race, family history of osteoporosis, early menopause, thin/small frame, inactive lifestyle, tobacco abuse). Those enrolled into Substudy II had to be 1–5 years postmenopausal with at least one additional risk factor for osteoporosis. A total of 3,397 women age 40–75 (mean age of 56 years) were enrolled in the overall study. Substudy I enrolled a total of 1,454 women (182 women receiving DUAVEE) with mean baseline T-scores of -1.43 and -1.52 in the DUAVEE and placebo groups, respectively. Substudy II enrolled a total of 861 women (with 111 women receiving DUAVEE) with mean baseline T-scores of -0.81 and -0.94 in the DUAVEE and placebo groups, respectively. Women also took calcium (600–1200 mg) and vitamin D (200–400 IU) daily.

In these substudies, treatment with DUAVEE significantly increased lumbar spine bone mineral density (BMD) at 24 months compared to placebo in both groups of postmenopausal women (Table 4).

Table 4: Lumbar Spine Bone Mineral Density Results at 24 Months (Study 1)
 | DUAVEE | Placebo
Between 1 and 5 Years Postmenopausal
N | 95 | 95
% Mean Change | 1.72 | -1.90
Difference from Placebo (95% C.I.) | 3.62 (2.64, 4.60) [p-value < 0.001]
More Than 5 Years Postmenopausal
N | 155 | 151
% Mean Change | 1.64 | -1.47
Difference from Placebo (95% C.I.) | 3.11 (2.29, 3.93) | –
** Adjusted mean changes, confidence intervals, and p-values based on an ANCOVA model with treatment and region (U.S. or non-U.S.) as factors and baseline BMD value and years since menopause as covariates using the Modified Intention to Treat population with Last Observation Carried Forward. Study 1 excludes those subjects with missing source documentation.

In Study 1, treatment with DUAVEE also significantly increased total hip BMD. The treatment difference (or difference from placebo) in total hip BMD at 24 months was 1.96% (DUAVEE minus placebo) in women who had been postmenopausal between 1 and 5 years and 1.73% (DUAVEE minus placebo) in women who had been postmenopausal for more than 5 years.

Study 2 was a 12-month, double-blind, randomized, placebo- and active-controlled study. The primary endpoint was the incidence of endometrial hyperplasia at 12 months. The prevention of osteoporosis was assessed in a substudy that enrolled women (n=590) who were less than 5 years postmenopausal (mean 2.5 years). The mean baseline T-score in the substudy was -0.91 in the DUAVEE group and -0.95 in the placebo group. The mean age of women (n=135) taking DUAVEE was 53 years (range 46–60 years). Women also took calcium (600 mg) and vitamin D (400 IU) daily.

In Study 2, treatment with DUAVEE significantly increased mean lumbar spine BMD (treatment difference, 1.51%), at 12 months compared to placebo in women who had been postmenopausal between 1 and 5 years. Treatment with DUAVEE also increased total hip BMD. The treatment difference in total hip BMD at 12 months was 1.21%.

14.3 Effects on the Endometrium

Effects of DUAVEE on endometrial hyperplasia and endometrial malignancy were assessed in Study 1 and Study 2. The Efficacy Evaluable population included patients who had taken at least one dose of DUAVEE, had baseline and post baseline endometrial biopsies, or had been diagnosed with hyperplasia. By endometrial biopsy, the incidence of endometrial hyperplasia or malignancy for DUAVEE was below 1% in both studies (see Table 5).

Table 5: Incidence of Endometrial Hyperplasia or Malignancy at Month 12 and Month 24
 |  | STUDY 1 [= Efficacy Evaluable population] |  | STUDY 2
Treatment Group | Month | % (n/N) | 1 – Sided 95% UL | % (n/N) | 1 – Sided 95% UL
DUAVEE | 12 | 0.00% (0/336) | 0.89 | 0.30% (1/335) | 1.41
DUAVEE | 24 | 0.68% (2/294) | 2.13 | -- | --
UL = Upper limit

14.4 Effects on Uterine Bleeding and Spotting

Uterine bleeding or spotting were evaluated in two clinical studies (Studies 1 and 2) by daily diary. In Study 1, cumulative amenorrhea at Year 1 was 83% in women treated with DUAVEE and 85% in women who received placebo. In Study 2, cumulative amenorrhea at Year 1 was 88% in women treated with DUAVEE and 84% in women who received placebo.

14.5 Women's Health Initiative Studies

The WHI enrolled approximately 11,000 predominantly healthy postmenopausal women to assess the risks and benefits of daily oral conjugated estrogens 0.625 mg compared to placebo in the prevention of certain chronic diseases. The primary endpoint was the incidence of CHD (defined as nonfatal MI, silent MI and CHD death), with invasive breast cancer as the primary adverse outcome. A "global index" included the earliest occurrence of CHD, invasive breast cancer, stroke, PE, colorectal cancer, hip fracture, or death due to other cause. These substudies did not evaluate the effects of conjugated estrogens on menopausal symptoms.

The WHI estrogen-alone substudy was stopped early because an increased risk of stroke was observed, and it was deemed that no further information would be obtained regarding the risks and benefits of estrogen-alone in predetermined primary endpoints.

Results of the estrogen-alone substudy, which included 10,739 women (average 63 years of age, range 50 to 79; 75.3 percent White, 15.1 percent Black, 6.1 percent Hispanic, 3.6 percent Other), after an average follow- up of 7.1 years are presented in Table 6.

Table 6: Relative and Absolute Risk Seen in the Estrogen Alone Substudy of WHI [Adapted from numerous WHI publications. WHI publications can be viewed at www.nhlbi.nih.gov/whi.]
Event | Relative Risk CE vs. Placebo (95% nCI [Nominal confidence intervals unadjusted for multiple looks and multiple comparisons.]) | CE n = 5,310 | Placebo N = 5,429
Event | Relative Risk CE vs. Placebo (95% nCI [Nominal confidence intervals unadjusted for multiple looks and multiple comparisons.]) | Absolute Risk per 10,000 Women-Years
CHD events [Results are based on centrally adjudicated data for an average follow-up of 7.1 years.] | 0.95 (0.78–1.16) | 54 | 57
Non-fatal MI | 0.91 (0.73–1.14) | 40 | 43
CHD death | 1.01 (0.71–1.43) | 16 | 16
All strokes | 1.33 (1.15–1.68) | 45 | 33
Ischemic stroke | 1.55 (1.19–2.01) | 38 | 25
Deep vein thrombosis, [Not included in "global index".] | 1.47 (1.06–2.06) | 23 | 15
Pulmonary embolism | 1.37 (0.90–2.07) | 14 | 10
Invasive breast cancer | 0.80 (0.62–1.04) | 28 | 34
Colorectal cancer [Results are based on an average follow-up of 6.8 years.] | 1.08 (0.75–1.55) | 17 | 16
Hip fracture | 0.65 (0.45–0.94) | 12 | 19
Vertebral fractures, | 0.64 (0.44–0.93) | 11 | 18
Lower arm/wrist fractures, | 0.58 (0.47–0.72) | 35 | 59
Total fractures, | 0.71 (0.64–0.80) | 144 | 197
Death due to other causes, [All deaths, except from breast or colorectal cancer, definite or probable CHD, PE, or cerebrovascular disease.] | 1.08 (0.88–1.32) | 53 | 50
Overall mortality, | 1.04 (0.88–1.22) | 79 | 75
Global Index [A subset of the events was combined in a "global index", defined as the earliest occurrence of CHD events, invasive breast cancer, stroke, PE, endometrial cancer, colorectal cancer, hip fracture, or death due to other causes.] | 1.02 (0.92–1.13) | 206 | 201

For those outcomes included in the WHI "global index" that reached statistical significance, the absolute excess risk per 10,000 women-years in the group treated with CE-alone was 12 more strokes, while the absolute risk reduction per 10,000 women-years was 7 fewer hip fractures. The absolute excess risk of events included in the "global index" was a non-significant 5 events per 10,000 women-years. There was no difference between the groups in terms of all-cause mortality.

No overall difference for primary CHD events (nonfatal MI, silent MI and CHD death) and invasive breast cancer incidence in women receiving conjugated estrogens-alone compared to placebo was reported in final centrally adjudicated results from the estrogen-alone substudy, after an average follow-up of 7.1 years.

Centrally adjudicated results for stroke events from the estrogen-alone substudy, after an average follow-up of 7.1 years, reported no significant differences in distribution of stroke subtype or severity, including fatal strokes, in women receiving conjugated estrogens-alone compared to placebo. Estrogen-alone increased the risk for ischemic stroke, and this excess risk was present in all subgroups of women examined.

Timing of the initiation of estrogen-alone therapy relative to the start of menopause may affect the overall risk benefit profile. The WHI estrogen-alone substudy, stratified by age, showed in women 50 to 59 years of age a non-significant trend toward reduced risk for CHD [hazard ratio (HR) 0.63 (95 percent CI, 0.36–1.09)] and overall mortality [HR 0.71 (95 percent CI, 0.46–1.11)].

14.6 Women's Health Initiative Memory Study

The WHIMS estrogen-alone ancillary study of WHI enrolled 2,947 predominantly healthy hysterectomized postmenopausal women 65 to 79 years of age (45 percent were 65 to 69 years of age, 36 percent were 70 to 74 years of age, and 19 percent were 75 years of age and older) to evaluate the effects of daily conjugated estrogens (0.625 mg)-alone on the incidence of probable dementia (primary outcome) compared to placebo.

After an average follow-up of 5.2 years, the relative risk of probable dementia for conjugated estrogens-alone versus placebo was 1.49 (95 percent CI, 0.83–2.66). The absolute risk of probable dementia for conjugated estrogens-alone versus placebo was 37 versus 25 cases per 10,000 women-years. Probable dementia as defined in this study included Alzheimer's disease (AD), vascular dementia (VaD) and mixed type (having features of both AD and VaD). The most common classification of probable dementia in the treatment group and the placebo group was AD. Since the ancillary study was conducted in women 65 to 79 years of age, it is unknown whether these findings apply to younger postmenopausal women [see Warnings and Precautions (5.4) and Use in Specific Populations (8.5)].

16 HOW SUPPLIED/STORAGE AND HANDLING

DUAVEE tablets contain 0.45 mg conjugated estrogens and 20 mg bazedoxifene. The tablets are oval, biconvex, and pink, branded with "0.45/20" in black ink on one side.

DUAVEE® tablets are supplied as follows:

 | Package | NDC number
Conjugated estrogens 0.45 mg/bazedoxifene 20 mg | 2 blisters of 15 tablets each | NDC 0008-1123-12

Storage

Blisters

DUAVEE tablets should be stored at 20°C to 25°C (68°F to 77°F); excursions permitted to 15°C to 30°C (59°F to 86°F). See USP Controlled Room Temperature. Dispense product in the original package. Tablets should not be removed from blisters until immediately before use. Protect from moisture. After opening foil pouch, product must be used within 60 days.

17 PATIENT COUNSELING INFORMATION

Advise the patient to read the FDA-approved patient labeling (Patient Information).

17.1 Instructions for Patients

- Keep DUAVEE in the original container to protect from moisture. Do not place DUAVEE in pill boxes or pill organizers.
- If more than one blister package is dispensed to the patient, instruct them to open one foil pouch at a time.
- Instruct patient to record the date the blister package is opened in the space provided on the blister package label. Do not use if the blister package has been open more than 60 days.
- Instruct patient to remove only one tablet from the blister package at the time of use.

17.2 Venous Thromboembolic Events

Advise patients to immediately report to their physician any signs or symptoms related to venous thrombosis and thromboembolic events [see Warnings and Precautions (5.2)].

17.3 Abnormal Vaginal Bleeding

Inform postmenopausal women of the importance of reporting abnormal vaginal bleeding to their healthcare provider as soon as possible [see Warnings and Precautions (5.3)].

17.4 Possible Serious Adverse Reactions with Estrogen Therapy

Inform postmenopausal women of possible serious adverse reactions of estrogen therapy including Cardiovascular Disorders, Malignant Neoplasms, and Probable Dementia [see Warnings and Precautions (5.2, 5.3, 5.4)].

17.5 Possible Less Serious Adverse Reactions with DUAVEE

Inform postmenopausal women of possible less serious but common adverse reactions of DUAVEE therapy such as muscle spasms, nausea, diarrhea, dyspepsia, upper abdominal pain, throat pain, dizziness and neck pain.

17.6 Calcium and Vitamin D Intake

Advise patients to add supplemental calcium and/or vitamin D to the diet if daily intake is inadequate.

This product's labeling may have been updated. For the most recent prescribing information, please visit www.pfizer.com.

LAB-0582-9.0

Patient Information DUAVEE® (DEW' ah-vee) (conjugated estrogens/bazedoxifene) Tablets

Read this Patient Information before you start taking DUAVEE and each time you get a refill. There may be new information. This information does not take the place of talking to your healthcare provider about your medical condition or your treatment.

What is the most important information I should know about DUAVEE?

- Do not take additional estrogen products while you are taking DUAVEE.
- Using estrogen-alone may increase your chance of getting cancer of the uterus (womb).
- Report any unusual vaginal bleeding right away while you are taking DUAVEE. Vaginal bleeding after menopause may be a warning sign of cancer of the uterus (womb). Your healthcare provider should check any unusual vaginal bleeding to find out the cause.
- Do not use estrogens to prevent heart disease, heart attacks, strokes or dementia (decline in brain function).
- Using estrogen-alone may increase your chances of getting strokes or blood clots.
- Using estrogen-alone may increase your chances of getting dementia, based on a study of women 65 years of age or older.
- The risks listed above are based on a study of an estrogen-alone oral product. Since other products and doses have not been studied in the same way, it is not known how the use of DUAVEE will affect your chances of getting these conditions. You and your healthcare provider should talk regularly about whether you still need treatment with DUAVEE.

What is DUAVEE?

DUAVEE is a prescription medicine that contains a mixture of estrogens and bazedoxifene.

What is DUAVEE used for?

DUAVEE is used after menopause for women with a uterus to:

- reduce moderate to severe hot flushes
  Estrogens are hormones made by a woman's ovaries. The ovaries normally stop making estrogens when a woman is between 45 and 55 years old. This drop in body estrogen levels causes the "change of life" or menopause (the end of monthly menstrual periods). Sometimes both ovaries are removed during an operation before natural menopause takes place. The sudden drop in estrogen levels causes "surgical menopause."
  When the estrogen levels begin dropping, some women get very uncomfortable symptoms, such as feelings of warmth in the face, neck, and chest, or sudden intense episodes of heat and sweating ("hot flashes" or "hot flushes"). In some women, the symptoms are mild, and they will not need to take medicines. In other women, symptoms can be more severe.
- help reduce your chances of developing osteoporosis (thin, weak bones)
  If you use DUAVEE only to prevent osteoporosis due to menopause, talk with your healthcare provider about whether a different treatment or medicine without estrogens might be better for you.
  DUAVEE should be taken for the shortest time possible and only for as long as treatment is needed.

You and your healthcare provider should talk regularly about whether you still need treatment with DUAVEE.

DUAVEE is not for use in children.

It is not known if DUAVEE is safe and effective in people with kidney problems.

Who should not take DUAVEE?

Do not take DUAVEE if you:

- currently have or have had blood clots
- are allergic to estrogens or bazedoxifene, the active ingredients in DUAVEE, or any of its ingredients.
  See the list of ingredients in DUAVEE at the end of this leaflet.
- have unusual vaginal bleeding. Vaginal bleeding after menopause may be a warning sign of cancer of the uterus (womb). Your healthcare provider should check any unusual vaginal bleeding to find out the cause.
- currently have or have had certain cancers. Estrogens may increase the chances of getting certain types of cancers, including cancer of the breast or uterus. If you have or have had cancer, talk with your healthcare provider about whether you should use DUAVEE.
- currently have or have had liver problems
- have been diagnosed with a bleeding disorder
- are pregnant. DUAVEE is not for pregnant women. If you think you may be pregnant, you should have a pregnancy test and know the results. Do not take DUAVEE if the test is positive and talk to your healthcare provider.

What should I tell my healthcare provider before taking DUAVEE?

Before you take DUAVEE, tell your healthcare provider if you:

- have any unusual vaginal bleeding.
- have any other medical conditions. Your healthcare provider may need to check you more carefully if you have certain conditions, such as asthma (wheezing), epilepsy (seizures), diabetes, migraine, endometriosis, lupus, or problems with your heart, liver, thyroid, kidneys, or have high calcium levels in your blood.
- are going to have surgery or will be on bed rest. Your healthcare provider will let you know if you need to stop taking DUAVEE.

Tell your healthcare provider about all the medicines you take, including prescription and over-the-counter medicines, vitamins, and herbal supplements.

Especially tell your healthcare provider if you take other hormonal medicines, including progestins or other medicines like DUAVEE. Ask your healthcare provider if you do not know if you take any of these medicines.

Some medicines may affect how DUAVEE works. DUAVEE may also affect how your other medicines work. Keep a list of your medicines and show it to your healthcare provider and pharmacist when you get a new medicine.

How should I take DUAVEE?

- DUAVEE comes in a blister package.
- Record the date you open the foil pouch in the space provided on the blister package label. Do not use if the blister package has been open for more than 60 days.
- Take DUAVEE exactly as your healthcare provider tells you to take it.
- Take 1 DUAVEE tablet at the same time each day.
- DUAVEE should be swallowed whole.
- Take DUAVEE with or without food.
- You should not remove DUAVEE from the blister until right before you are ready to take it. Remove 1 tablet at a time from the blister package. Do not place DUAVEE in pill boxes or pill organizers.
- If you miss a dose of DUAVEE, take it as soon as you remember. If it is almost time for your next dose, skip the missed dose. Take the next dose at your regular time. Do not take 2 doses at the same time unless your healthcare provider tells you to. If you are not sure about your dosing, call your healthcare provider.
- If you take a calcium or vitamin D supplement, you may take it at the same time you take DUAVEE.
- If you take too much DUAVEE, call your healthcare provider. Symptoms of taking too much DUAVEE include:

  - nausea
  - vomiting
  - breast tenderness
  - dizziness

  - abdominal pain
  - feeling tired
  - vaginal bleeding

What are the possible side effects of DUAVEE?

Side effects are grouped by how serious they are and how often they happen when you are treated.

Serious side effects include:

- blood clots
- stroke
- heart attack
- cancer of the lining of the uterus
- breast cancer
- cancer of the ovary
- dementia
- gallbladder problems
- loss of vision
- high blood pressure
- increased fats in your blood
- liver problems
- thyroid problems
- fluid retention
- low calcium
- swelling of your mouth or tongue
- worsening of other medical problems such as asthma, diabetes, epilepsy, migraines, a genetic problem called porphyria, lupus and liver problems

Call your healthcare provider right away if you get any of the following warning signs, or any other unusual symptoms that concern you:

- new breast lumps
- unusual vaginal bleeding
- changes in vision or speech
- sudden new severe headaches
- severe pains in your chest or legs with or without shortness of breath, weakness and fatigue

Less serious, but common side effects include:

- muscle spasms
- nausea
- diarrhea
- upset stomach
- abdominal pain
- throat pain
- dizziness
- neck pain

These are not all the possible side effects of DUAVEE. For more information, ask your healthcare provider or pharmacist. Tell your healthcare provider if you have any side effects that bother you or do not go away.

Call your doctor for medical advice about side effects. You may report side effects to FDA at 1-800-FDA-1088.

What can I do to lower my chances of a serious side effect with DUAVEE?

- Talk with your healthcare provider regularly about whether you should continue taking DUAVEE.
- See your healthcare provider right away if you get vaginal bleeding while taking DUAVEE.
- Have a pelvic exam, breast exam and mammogram (breast X-ray) every year unless your healthcare provider tells you something else.
- If members of your family have had breast cancer or if you have ever had breast lumps or an abnormal mammogram, you may need to have breast exams more often.
- If you have high blood pressure, high cholesterol (fat in the blood), diabetes, are overweight, or if you use tobacco, you may have higher chances of getting heart disease.

Ask your healthcare provider for ways to lower your chances of getting heart disease.

How do I store DUAVEE?

- Store DUAVEE at room temperature between 68°F to 77°F (20°C to 25°C).
- Keep DUAVEE in the blister until you are ready to take it to protect the tablet from moisture.
- Do not place DUAVEE in pill boxes or pill organizers.
- After opening the foil pouch the DUAVEE blisters come in, DUAVEE must be used within 60 days.

Keep DUAVEE and all other medicines out of the reach of children.

General information about the safe and effective use of DUAVEE

Medicines are sometimes prescribed for purposes other than those listed in a Patient Information leaflet. Do not use DUAVEE for a condition for which it was not prescribed. Do not give DUAVEE to other people, even if they have the same symptoms you have. It may harm them.

This Patient Information summarizes the most important information about DUAVEE. If you would like more information, talk with your healthcare provider. You can ask your pharmacist or healthcare provider for information about DUAVEE that is written for health professionals.

What are the ingredients in DUAVEE?

Active Ingredients: conjugated estrogens and bazedoxifene. Conjugated estrogens are a mixture of sodium estrone sulfate and sodium equilin sulfate and other components, including sodium sulfate conjugates, 17α-dihydroequilin, 17α-estradiol, and 17β-dihydroequilin.

Inactive Ingredients: calcium phosphate tribasic, hydroxypropyl cellulose, microcrystalline cellulose, powdered cellulose, hypromellose, lactose monohydrate, magnesium stearate, polyethylene glycol, sucrose, ascorbic acid, sucrose palmitic acid ester, hydroxyethylcellulose, titanium dioxide, red iron oxide, yellow iron oxide, black iron oxide, povidone, polydextrose, maltitol, poloxamer 188, propylene glycol, isopropyl alcohol.

This Patient Information has been approved by the U.S. Food and Drug Administration.

This product's labeling may have been updated. For the most recent prescribing information, please visit www.pfizer.com or call 1-800-438-1985.

LAB-0583-6.0
Revised December 2022

PRINCIPAL DISPLAY PANEL - 15 Tablet Blister Pack

NDC 0008-1123-12

Pfizer

Duavee®

(conjugated estrogens/
bazedoxifene)
tablets

per tablet

0.45 mg/20 mg*

*Each tablet contains bazedoxifene
equivalent to 22.6 mg of
bazedoxifene acetate

15 tablets

After opening foil pouch, product must be used within 60 days.

Date foil pouch opened:
Store at 20°C to 25°C (68°F to 77°F); excursions permitted to
15°C to 30°C (59°F to 86°F) [see USP Controlled Room Temperature].
DOSAGE AND USE: See accompanying prescribing information.
Store product in original package to keep from moisture.
Tablets should not be removed from blisters until immediately
before administration. Do not place medication in pill boxes.

Distributed by
Wyeth Pharmaceuticals LLC
A subsidiary of Pfizer Inc.
Philadelphia, PA 19101
MADE IN IRELAND

Rx only

PAA195314

LOT:
EXP:

PRINCIPAL DISPLAY PANEL - 30 Tablet Blister Pack Pouch

NDC 0008-1123-12

Pfizer

Duavee®

(conjugated estrogens/
bazedoxifene)
tablets

0.45 mg/20 mg*

After opening foil pouch, product must be used
within 60 days.

Dispense and store product in original package
to protect from moisture.

30 tablets

Rx only

Package includes 2 blister cards
containing 15 tablets each.

PRINCIPAL DISPLAY PANEL - 30 Tablet Blister Pack Pouch Carton

NDC 0008-1123-12

Pfizer

Duavee®

(conjugated estrogens/
bazedoxifene)
tablets

0.45 mg/20 mg*

After opening foil pouch, product must be used
within 60 days.

Dispense and store product in original package
to protect from moisture.

30 tablets

Rx only

Package includes 2 blister cards
containing 15 tablets each.